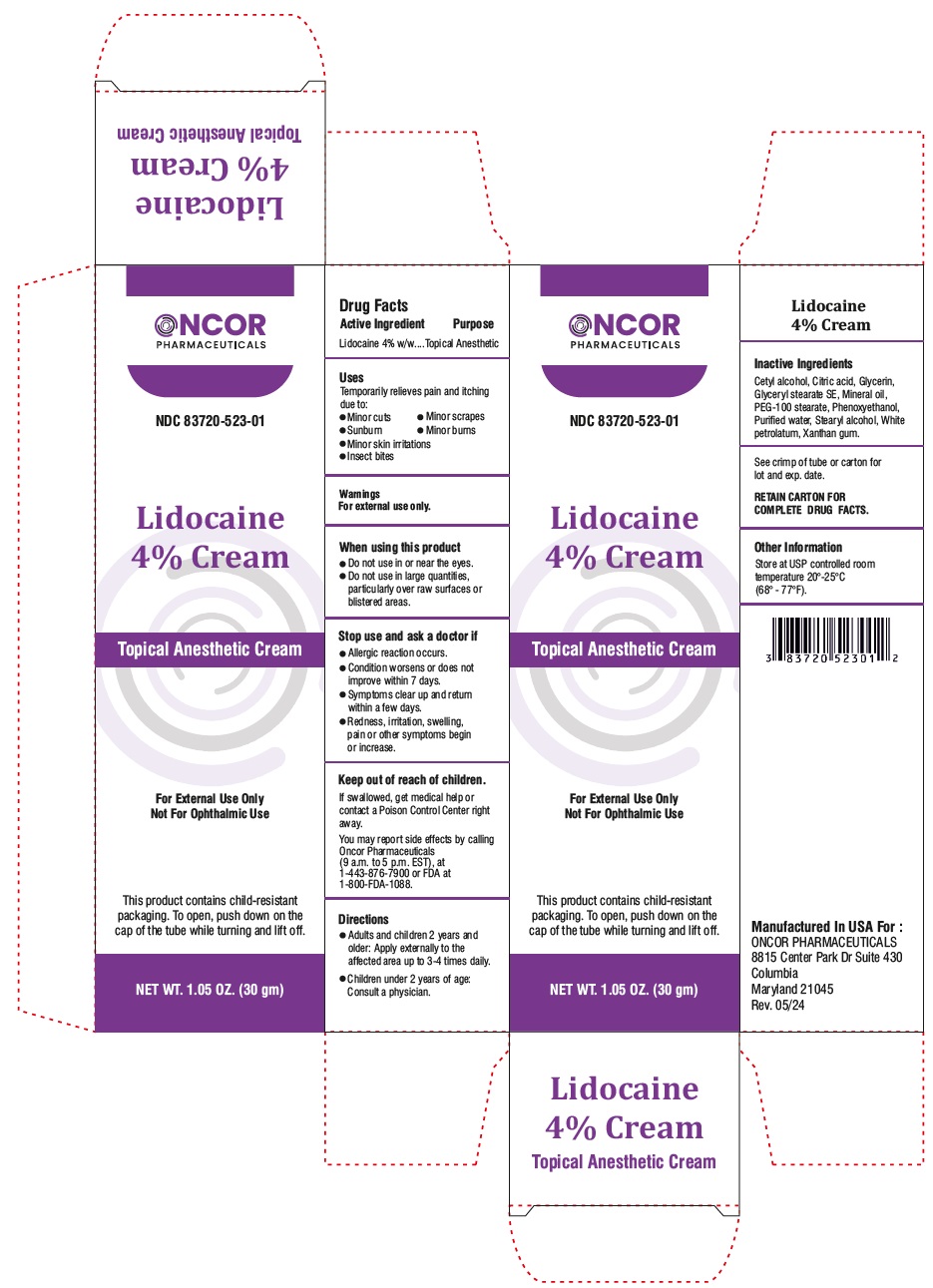 DRUG LABEL: Lidocaine 4% Topical Anesthetic Cream
NDC: 83720-523 | Form: CREAM
Manufacturer: Oncor Pharmaceuticals
Category: otc | Type: HUMAN OTC DRUG LABEL
Date: 20260105

ACTIVE INGREDIENTS: LIDOCAINE 4 g/100 g
INACTIVE INGREDIENTS: CETYL ALCOHOL; CITRIC ACID ACETATE; MINERAL OIL; WATER; WHITE PETROLATUM; GLYCERIN; GLYCERYL STEARATE SE; PEG-100 STEARATE; PHENOXYETHANOL; STEARYL ALCOHOL; XANTHAN GUM

Lidocaine 4% Cream

Drug Facts Active Ingredients

Lidocaine 4% w/w

Purpose

Topical Anesthetic

Uses

Temporarily relieves pain and itching due to:

- Minor cuts
- Minor scrapes
- Sunburn
- Minor burns
- Minor skin irritations
- Insect bites

Warnings

For external use only.

When using this product

- Do not use in or near the eyes.
- Do not use in large quantities, particularly over raw surfaces or blistered areas.

Stop use and ask a doctor if

- Allergic reaction occurs.
- Condition worsens or does not improve within 7 days.
- Symptoms clear up and return within a few days.
- Redness, irritation, swelling, pain or other symptoms begin or increase.

Keep out of reach of children

If swallowed, get medical help or contact a Poison Control Center right away.

You may report side effects by calling Oncor Pharmaceuticals (9 a.m. to 5 p.m. EST), at 1-443-876-7900 or FDA at 1-800-FDA-1088.

Directions

- Adults and children 2 years and older: apply externally to the affected area up to 3-4 times daily.
- Children under 2 years of age: consult a physician.

Inactive Ingredients

Cetyl alcohol, Citric acid, Glycerin, Glyceryl stearate SE, Mineral oil, PEG-100 stearate, Phenoxyethanol, Purified water, Stearyl alcohol, White
petrolatum, Xanthan gum.

See crimp of tube or carton for lot and exp. date.

RETAIN CARTON FOR COMPLETE DRUG FACTS.

Other information

Store at USP controlled room temperature 20°-25°C (68°-77°F).

Manufactured In USA For :

ONCOR PHARMACEUTICALS
8815 Center Park Dr Suite 430
Columbia
Maryland 21045

Package Label

ONCOR PHARMACEUTICALS

NDC 83720- 523-01

Lidocaine 4% Cream

Topical Anesthetic Cream

For External Use Only
Not For Ophthalmic Use

This product contains child-resistant
packaging. To open, push down on the cap of the tube while turning and lift off.

NET WT. 1.05 OZ. (30 gm)